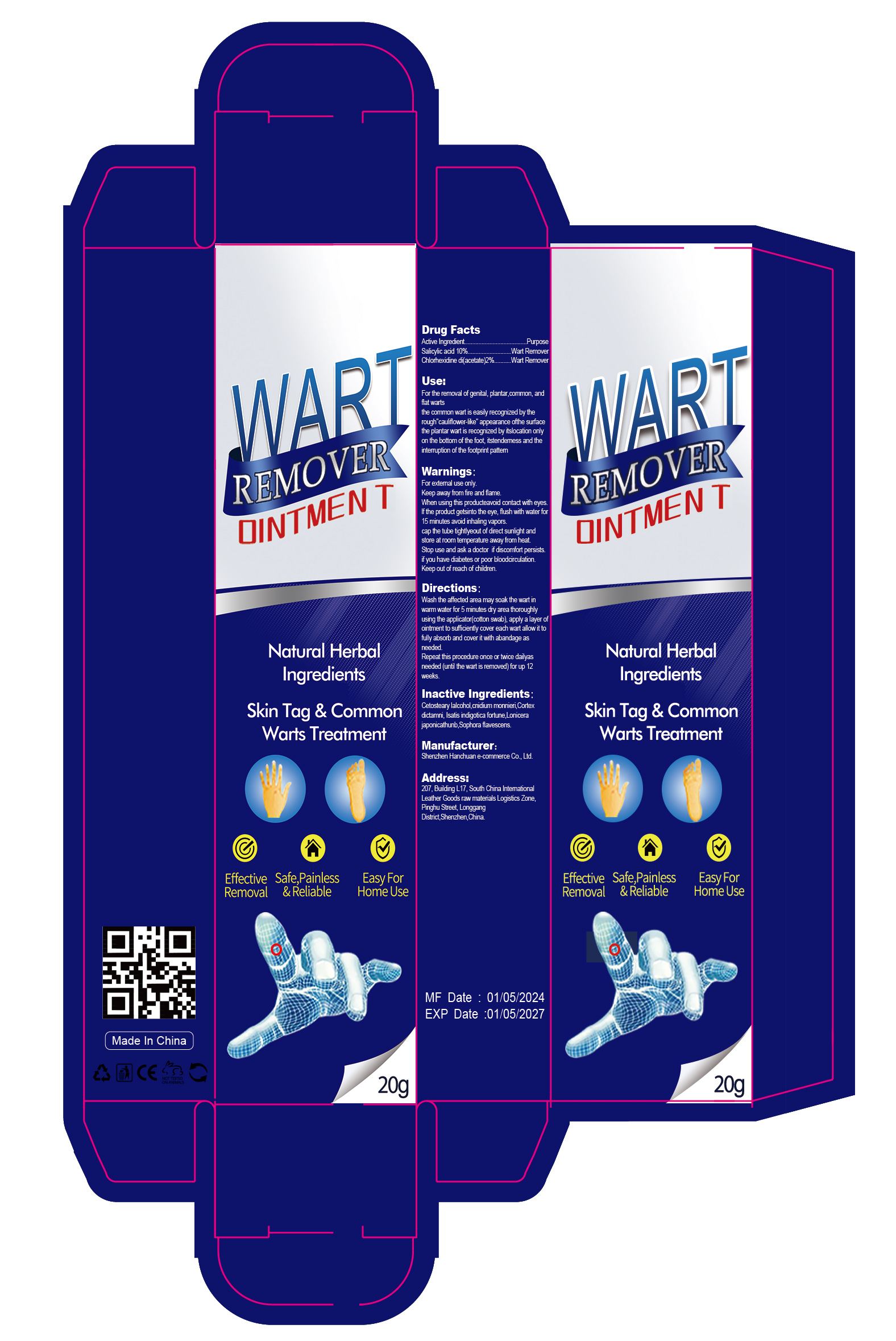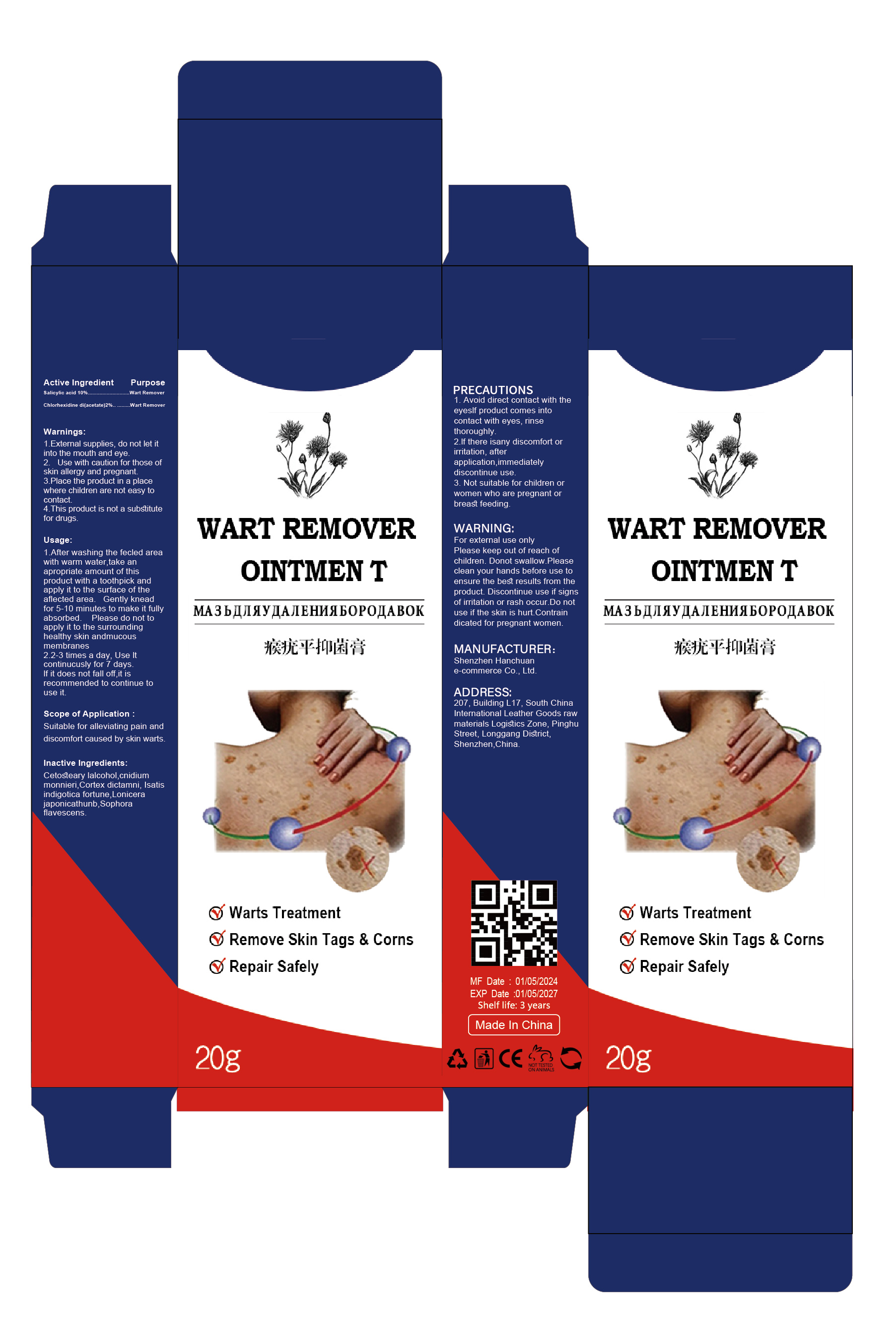 DRUG LABEL: Wart Remover Ointmen t
NDC: 84302-006 | Form: OINTMENT
Manufacturer: Shenzhen Hanchuan e-commerce Co., Ltd
Category: otc | Type: HUMAN OTC DRUG LABEL
Date: 20240517

ACTIVE INGREDIENTS: ACETATE ION 2 g/100 g; SALICYLIC ACID 10 g/100 g
INACTIVE INGREDIENTS: CNIDIUM MONNIERI WHOLE; DICTAMNUS DASYCARPUS WHOLE; ISATIS TINCTORIA WHOLE; SOPHORA FLAVESCENS WHOLE; CETOSTEARYL ALCOHOL; LONICERA JAPONICA WHOLE

Wart Remover Ointment

ACTIVE INGREDIENT

Salicylic acid 10%
Chlorhexidine di(acetate) 2%

PURPOSE

Wart Remover

KEEP OUT OF REACH OF CHILDREN SECTION

INDICATIONS AND USAGE

For the removal of genital, plantar,common, andflat warts
the common wart is easily recognized by therough cauliflower-ike" appearance ofthe surfacethe plantar wart is recognized by itslocation onlyon the bottom of the foot, itstendemess and theintemuption of the footprint pattem

WARNINGS

For extemal use only
Keep away from fire and flame.
When using this producteavoid contact with eyeslf the product getsinto the eye, flush with water for15 m nutes avoid inha ing vapors.
cap the tube tightyeout of direct sunlight andstore at room temperature away from heat
Stop use and ask a doctor if discomfort persists
if you have diabetes or poor blooda rculation.
Keep out of reach of children.

DOSAGE AND ADMINISTRATION

Wash the aifected area may soak the wart inwamm water for 5 minutes dry area thoroughlyusing the applicator(cotton swab , apply a layer ofo ntment to sufficiently cover each wart allow it tofully absorb and cover it with abandage asneeded.
Repeat this procedure once or twice dailyasneeded (until the wart is removed) for up 12weeks.

INACTIVE INGREDIENT

Cetosteary lalcohol
cnidium monnieri
Cortex dictamni
Isatis indigotica fortune
Lonicera japonicathunb

Sophora flavescens